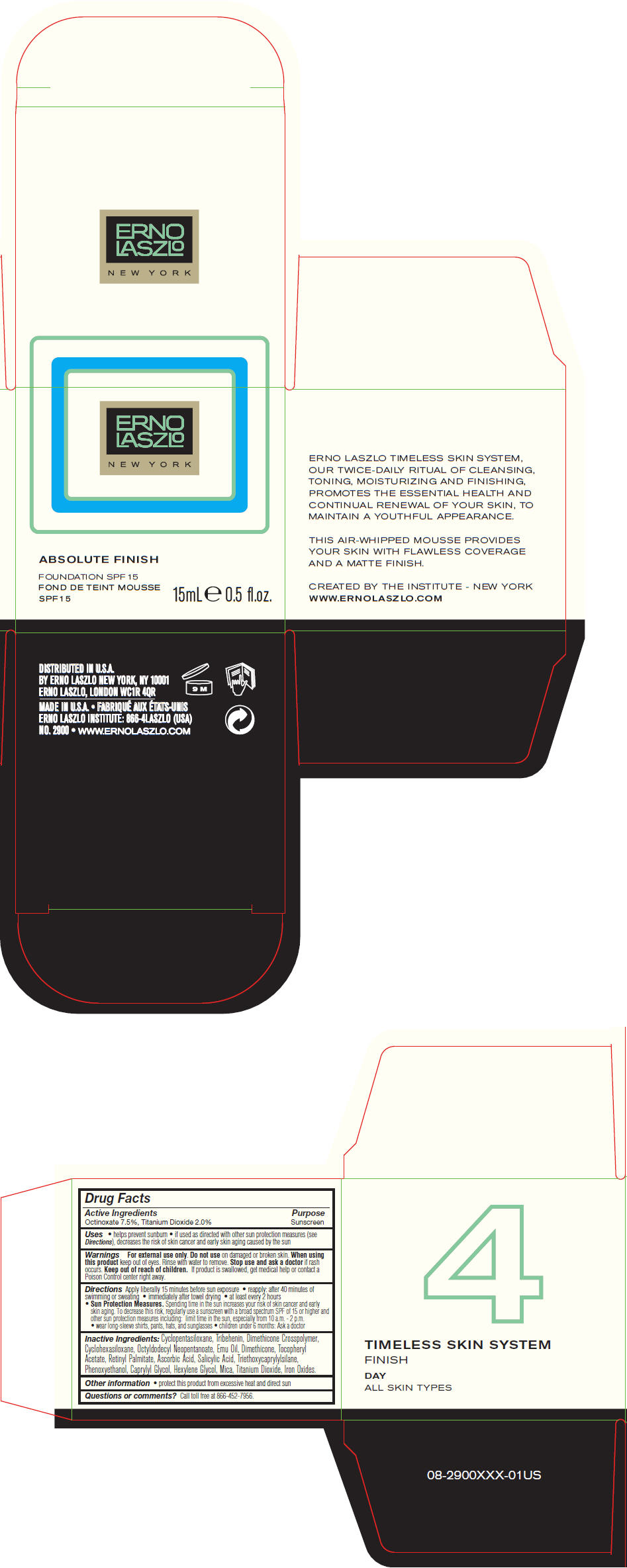 DRUG LABEL: Absolute Finish Foundation  SPF15
NDC: 57913-2900 | Form: LOTION
Manufacturer: Erno Laszlo, Inc.
Category: otc | Type: HUMAN OTC DRUG LABEL
Date: 20130408

ACTIVE INGREDIENTS: Octinoxate 75 mg/1 mL; Titanium Dioxide 20 mg/1 mL
INACTIVE INGREDIENTS: Cyclomethicone 5; Tribehenin; Cyclomethicone 6; Octyldodecyl Neopentanoate; Emu Oil; Dimethicone; .Alpha.-Tocopherol Acetate; Vitamin A Palmitate; Ascorbic Acid; Salicylic Acid; Triethoxycaprylylsilane; Phenoxyethanol; Caprylyl Glycol; Hexylene Glycol; Mica

Absolute Finish Foundation SPF15

Drug Facts

Active Ingredients

Octinoxate 7.5%, Titanium Dioxide 2.0%

Purpose

Sunscreen

Uses

- helps prevent sunburn
- if used as directed with other sun protection measures (see Directions), decreases the risk of skin cancer and early skin aging caused by the sun

Warnings

For external use only.

Do not use on damaged or broken skin.

When using this product keep out of eyes. Rinse with water to remove.

Stop use and ask a doctor if rash occurs.

Keep out of reach of children. If product is swallowed, get medical help or contact a Poison Control center right away.

Directions

Apply liberally 15 minutes before sun exposure

- reapply: after 40 minutes of swimming or sweating
- immediately after towel drying
- at least every 2 hours
- Sun Protection Measures. Spending time in the sun increases your risk of skin cancer and early skin aging. To decrease this risk, regularly use a sunscreen with a broad spectrum SPF of 15 or higher and other sun protection measures including: limit time in the sun, especially from 10 a.m. - 2 p.m.
  - wear long-sleeve shirts, pants, hats, and sunglasses
  - children under 6 months: Ask a doctor

Inactive Ingredients

Cyclopentasiloxane, Tribehenin, Dimethicone Crosspolymer, Cyclohexasiloxane, Octyldodecyl Neopentanoate, Emu Oil, Dimethicone, Tocopheryl Acetate, Retinyl Palmitate, Ascorbic Acid, Salicylic Acid, Triethoxycaprylylsilane, Phenoxyethanol, Caprylyl Glycol, Hexylene Glycol, Mica, Titanium Dioxide, Iron Oxides.

Other information

- protect this product from excessive heat and direct sun

Questions or comments?

Call toll free at 866-452-7956.

DISTRIBUTED IN U.S.A.
BY ERNO LASZLO NEW YORK, NY 10001

PRINCIPAL DISPLAY PANEL - 15 mL Jar Carton

ERNO
LASZLO

NEW YORK

ABSOLUTE FINISH

FOUNDATION SPF 15

15mL e 0.5 fl.oz.